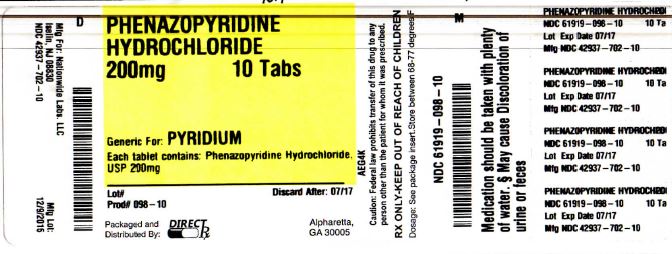 DRUG LABEL: PHENAZOPYRIDINE HYDROCHLORIDE
NDC: 61919-098 | Form: TABLET, COATED
Manufacturer: DirectRX
Category: prescription | Type: HUMAN PRESCRIPTION DRUG LABEL
Date: 20151209

ACTIVE INGREDIENTS: PHENAZOPYRIDINE HYDROCHLORIDE 200 mg/1 1
INACTIVE INGREDIENTS: MINERAL OIL; MAGNESIUM STEARATE; CELLULOSE, MICROCRYSTALLINE; STARCH, CORN; CROSCARMELLOSE SODIUM; HYPROMELLOSES; POVIDONES; PROPYLENE GLYCOL; SILICON DIOXIDE

PHENAZOPYRIDINE HYDROCHLORIDE